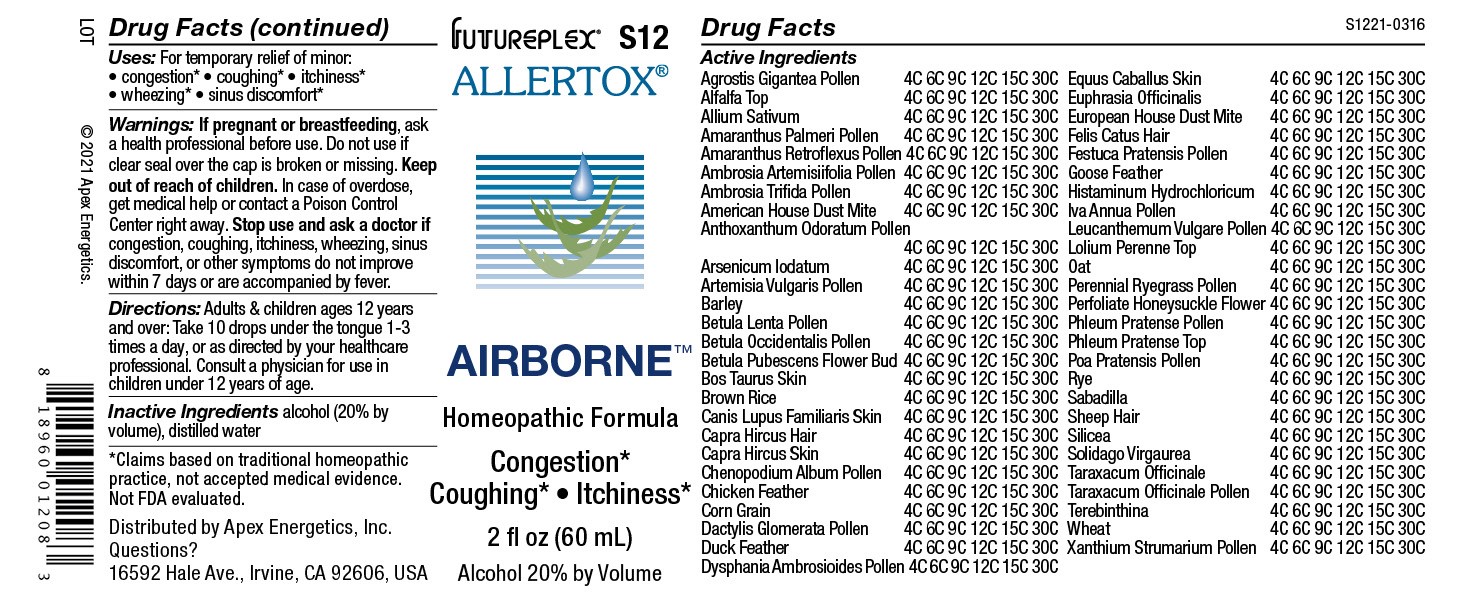 DRUG LABEL: S12
NDC: 63479-1912 | Form: SOLUTION/ DROPS
Manufacturer: Apex Energetics Inc.
Category: homeopathic | Type: HUMAN OTC DRUG LABEL
Date: 20240108

ACTIVE INGREDIENTS: ALFALFA TOP 30 [hp_C]/1 mL; AMARANTHUS PALMERI POLLEN 30 [hp_C]/1 mL; AMBROSIA ARTEMISIIFOLIA POLLEN 30 [hp_C]/1 mL; BARLEY 30 [hp_C]/1 mL; BETULA PUBESCENS FLOWER BUD 30 [hp_C]/1 mL; HISTAMINE DIHYDROCHLORIDE 30 [hp_C]/1 mL; RYE 30 [hp_C]/1 mL; SHEEP WOOL 30 [hp_C]/1 mL; IVA ANNUA POLLEN 30 [hp_C]/1 mL; LOLIUM PERENNE TOP 30 [hp_C]/1 mL; LONICERA CAPRIFOLIUM FLOWER 30 [hp_C]/1 mL; LOLIUM PERENNE POLLEN 30 [hp_C]/1 mL; TARAXACUM OFFICINALE 30 [hp_C]/1 mL; DERMATOPHAGOIDES PTERONYSSINUS 30 [hp_C]/1 mL; FESTUCA PRATENSIS POLLEN 30 [hp_C]/1 mL; LEUCANTHEMUM VULGARE POLLEN 30 [hp_C]/1 mL; BETULA LENTA POLLEN 30 [hp_C]/1 mL; CAPRA HIRCUS HAIR 30 [hp_C]/1 mL; WHEAT 30 [hp_C]/1 mL; AMARANTHUS RETROFLEXUS POLLEN 30 [hp_C]/1 mL; DERMATOPHAGOIDES FARINAE 30 [hp_C]/1 mL; PHLEUM PRATENSE POLLEN 30 [hp_C]/1 mL; SCHOENOCAULON OFFICINALE SEED 30 [hp_C]/1 mL; ANTHOXANTHUM ODORATUM POLLEN 30 [hp_C]/1 mL; BOS TAURUS SKIN 30 [hp_C]/1 mL; CANIS LUPUS FAMILIARIS SKIN 30 [hp_C]/1 mL; CAPRA HIRCUS SKIN 30 [hp_C]/1 mL; GARLIC 30 [hp_C]/1 mL; XANTHIUM STRUMARIUM POLLEN 30 [hp_C]/1 mL; FELIS CATUS HAIR 30 [hp_C]/1 mL; OAT 30 [hp_C]/1 mL; PHLEUM PRATENSE TOP 30 [hp_C]/1 mL; BROWN RICE 30 [hp_C]/1 mL; TURPENTINE OIL 30 [hp_C]/1 mL; CHENOPODIUM ALBUM POLLEN 30 [hp_C]/1 mL; ANSER ANSER FEATHER 30 [hp_C]/1 mL; ARSENIC TRIIODIDE 30 [hp_C]/1 mL; ARTEMISIA VULGARIS POLLEN 30 [hp_C]/1 mL; BETULA OCCIDENTALIS POLLEN 30 [hp_C]/1 mL; DACTYLIS GLOMERATA POLLEN 30 [hp_C]/1 mL; GALLUS GALLUS FEATHER 30 [hp_C]/1 mL; POA PRATENSIS POLLEN 30 [hp_C]/1 mL; CORN GRAIN 30 [hp_C]/1 mL; ANAS PLATYRHYNCHOS FEATHER 30 [hp_C]/1 mL; DYSPHANIA AMBROSIOIDES POLLEN 30 [hp_C]/1 mL; EQUUS CABALLUS SKIN 30 [hp_C]/1 mL; EUPHRASIA STRICTA 30 [hp_C]/1 mL; SILICON DIOXIDE 30 [hp_C]/1 mL; SOLIDAGO VIRGAUREA FLOWERING TOP 30 [hp_C]/1 mL; TARAXACUM OFFICINALE POLLEN 30 [hp_C]/1 mL; AGROSTIS GIGANTEA POLLEN 30 [hp_C]/1 mL; AMBROSIA TRIFIDA POLLEN 30 [hp_C]/1 mL
INACTIVE INGREDIENTS: ALCOHOL; WATER

S12

Active Ingredients
Agrostis Gigantea Pollen | 4C 6C 9C 12C 15C 30C
Alfalfa Top | 4C 6C 9C 12C 15C 30C
Allium Sativum | 4C 6C 9C 12C 15C 30C
Amaranthus Palmeri Pollen | 4C 6C 9C 12C 15C 30C
Amaranthus Retroflexus Pollen | 4C 6C 9C 12C 15C 30C
Ambrosia Artemisiifolia Pollen | 4C 6C 9C 12C 15C 30C
Ambrosia Trifida Pollen | 4C 6C 9C 12C 15C 30C
American House Dust Mite | 4C 6C 9C 12C 15C 30C
Anthoxanthum Odoratum Pollen | 4C 6C 9C 12C 15C 30C
Arsenicum Iodatum | 4C 6C 9C 12C 15C 30C
Artemisia Vulgaris Pollen | 4C 6C 9C 12C 15C 30C
Barley | 4C 6C 9C 12C 15C 30C
Betula Lenta Pollen | 4C 6C 9C 12C 15C 30C
Betula Occidentalis Pollen | 4C 6C 9C 12C 15C 30C
Betula Pubescens Flower Bud | 4C 6C 9C 12C 15C 30C
Bos Taurus Skin | 4C 6C 9C 12C 15C 30C
Brown Rice | 4C 6C 9C 12C 15C 30C
Canis Lupus Familiaris Skin | 4C 6C 9C 12C 15C 30C
Capra Hircus Hair | 4C 6C 9C 12C 15C 30C
Capra Hircus Skin | 4C 6C 9C 12C 15C 30C
Chenopodium Album Pollen | 4C 6C 9C 12C 15C 30C
Chicken Feather | 4C 6C 9C 12C 15C 30C
Corn Grain | 4C 6C 9C 12C 15C 30C
Dactylis Glomerata Pollen | 4C 6C 9C 12C 15C 30C
Duck Feather | 4C 6C 9C 12C 15C 30C
Dysphania Ambrosioides Pollen | 4C 6C 9C 12C 15C 30C
Equus Caballus Skin | 4C 6C 9C 12C 15C 30C
Euphrasia Officinalis | 4C 6C 9C 12C 15C 30C
European House Dust Mite | 4C 6C 9C 12C 15C 30C
Felis Catus Hair | 4C 6C 9C 12C 15C 30C
Festuca Pratensis Pollen | 4C 6C 9C 12C 15C 30C
Goose Feather | 4C 6C 9C 12C 15C 30C
Histaminum Hydrochloricum | 4C 6C 9C 12C 15C 30C
Iva Annua Pollen | 4C 6C 9C 12C 15C 30C
Leucanthemum Vulgare Pollen | 4C 6C 9C 12C 15C 30C
Lolium Perenne Top | 4C 6C 9C 12C 15C 30C
Oat | 4C 6C 9C 12C 15C 30C
Perennial Ryegrass Pollen | 4C 6C 9C 12C 15C 30C
Perfoliate Honeysuckle Flower | 4C 6C 9C 12C 15C 30C
Phleum Pratense Pollen | 4C 6C 9C 12C 15C 30C
Phleum Pratense Top | 4C 6C 9C 12C 15C 30C
Poa Pratensis Pollen | 4C 6C 9C 12C 15C 30C
Rye | 4C 6C 9C 12C 15C 30C
Sabadilla | 4C 6C 9C 12C 15C 30C
Sheep Hair | 4C 6C 9C 12C 15C 30C
Silicea | 4C 6C 9C 12C 15C 30C
Solidago Virgaurea | 4C 6C 9C 12C 15C 30C
Taraxacum Officinale | 4C 6C 9C 12C 15C 30C
Taraxacum Officinale Pollen | 4C 6C 9C 12C 15C 30C
Terebinthina | 4C 6C 9C 12C 15C 30C
Wheat | 4C 6C 9C 12C 15C 30C
Xanthium Strumarium Pollen | 4C 6C 9C 12C 15C 30C

INDICATIONS AND USAGE

Uses:

For temporary relief of minor:

congestion*

coughing*

itchiness*

wheezing*

sinus discomfort*

*Claims based on traditional homeopathic practice, not accepted medical evidence. Not FDA evaluated.

Warnings:

PREGNANCY OR BREAST FEEDING

If pregnant or breastfeeding, ask a health professional before use.

Do not use if clear seal over the cap is broken or missing.

Keep out of reach of children. In case of overdose, get medical help or contact a Poison Control Center right away.

Stop use and ask a doctor if congestion, coughing, itchiness, wheezing, sinus discomfort, or other symptoms do not improve within 7 days or are accompanied by fever.

Directions:

Adults & children ages 12 years and over: Take 10 drops under the tongue 1-3 times a day, or as directed by your healthcare professional. Consult a physician for use in children under 12 years of age.

Inactive Ingredients

alcohol (20% by volume), distilled water

Distributed by Apex Energetics, Inc.Questions?

16592 Hale Ave., Irvine, CA 92606, USA

PACKAGE LABEL

FUTUREPLEX® S12

ALLERTOX®

AIRBORNE™

Homeopathic Formula

Congestion*

Coughing*

Itchiness*

2 fl oz (60 mL)

Alcohol 20% by Volume